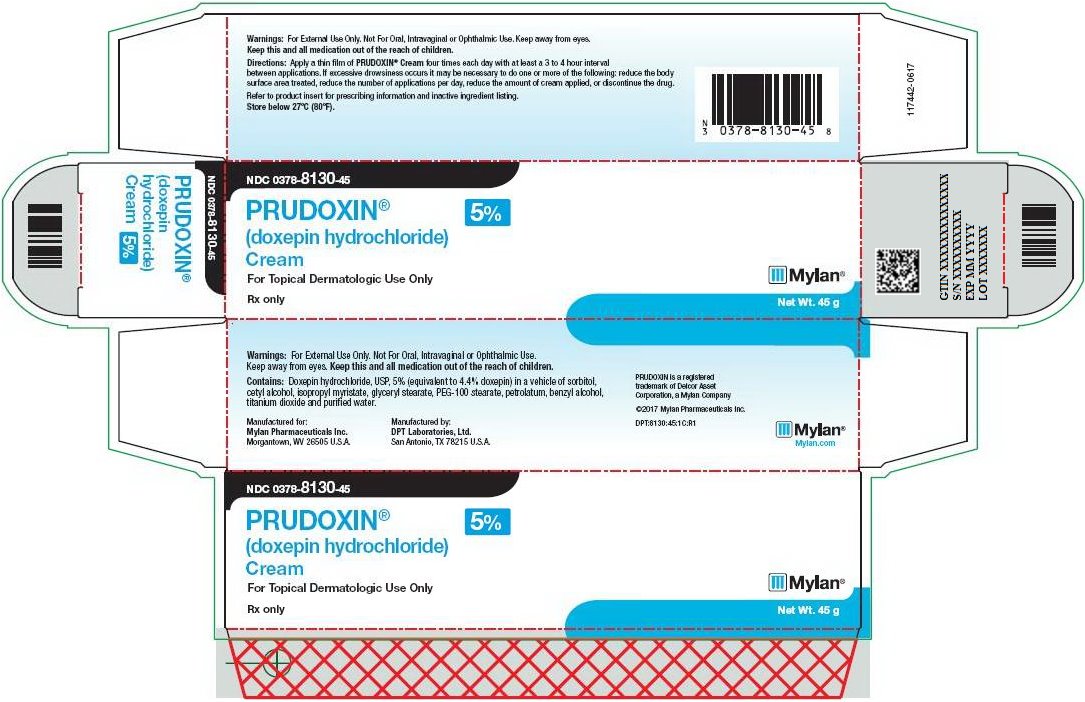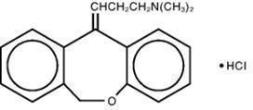 DRUG LABEL: PRUDOXIN
NDC: 0378-8130 | Form: CREAM
Manufacturer: Mylan Pharmaceuticals Inc.
Category: prescription | Type: HUMAN PRESCRIPTION DRUG LABEL
Date: 20170629

ACTIVE INGREDIENTS: DOXEPIN HYDROCHLORIDE 50 mg/1 g
INACTIVE INGREDIENTS: SORBITOL; CETYL ALCOHOL; ISOPROPYL MYRISTATE; GLYCERYL MONOSTEARATE; PEG-100 STEARATE; PETROLATUM; BENZYL ALCOHOL; TITANIUM DIOXIDE; WATER

Prudoxin

PRUDOXIN® doxepin hydrochloride cream
Prestium Pharma, Inc.

Rx only

PRUDOXIN® (doxepin hydrochloride) Cream, 5%

FOR TOPICAL DERMATOLOGIC USE ONLY — NOT FOR OPHTHALMIC, ORAL, OR INTRAVAGINAL USE.

DESCRIPTION

PRUDOXIN® (doxepin hydrochloride) Cream, 5% is a topical cream. Each gram contains: 50 mg of doxepin hydrochloride (equivalent to 44.3 mg of doxepin).

Doxepin hydrochloride, USP is one of a class of agents known as dibenzoxepin tricyclic antidepressant compounds. It is an isomeric mixture of N,N-dimethyldibenz[b,e]oxepin-Δ11(6H),γ-propylamine hydrochloride. Doxepin hydrochloride has a molecular formula of C19H21NO•HCl and a molecular weight of 316.

PRUDOXIN® Cream also contains sorbitol, cetyl alcohol, isopropyl myristate, glyceryl stearate, PEG- 100 stearate, petrolatum, benzyl alcohol, titanium dioxide and purified water.

CLINICAL PHARMACOLOGY

Although doxepin HCl does have H1 and H2 histamine receptor blocking actions, the exact mechanism by which doxepin exerts its antipruritic effect is unknown. PRUDOXIN® Cream can produce drowsiness which may reduce awareness, including awareness of pruritic symptoms. In 19 pruritic eczema patients treated with PRUDOXIN® Cream, plasma doxepin concentrations ranged from nondetectable to 47 ng/mL from percutaneous absorption. Plasma levels from topical application of PRUDOXIN® Cream can result in CNS and other systemic side effects.

Once absorbed into the systemic circulation, doxepin undergoes hepatic metabolism that results in conversion to pharmacologically-active desmethyldoxepin. Further glucuronidation results in urinary excretion of the parent drug and its metabolites. Desmethyldoxepin has a half-life that ranges from 28 to 52 hours and is not affected by multiple dosing. Plasma levels of both doxepin and desmethyldoxepin are highly variable and are poorly correlated with dosage. Wide distribution occurs in body tissues including lungs, heart, brain, and liver. Renal disease, genetic factors, age, and other medications affect the metabolism and subsequent elimination of doxepin. (See PRECAUTIONS - Drug Interactions.)

INDICATIONS AND USAGE

PRUDOXIN® Cream is indicated for the short-term (up to 8 days) management of moderate pruritus in adult patients with atopic dermatitis or lichen simplex chronicus. (See DOSAGE AND ADMINISTRATION.)

CONTRAINDICATIONS

Because doxepin HCl has an anticholinergic effect and because significant plasma levels of doxepin are detectable after topical PRUDOXIN® Cream application, the use of PRUDOXIN® Cream is contraindicated in patients with untreated narrow angle glaucoma or a tendency to urinary retention.

PRUDOXIN® Cream is contraindicated in individuals who have shown previous sensitivity to any of its components.

WARNINGS

Drowsiness occurs in over 20% of patients treated with PRUDOXIN® Cream, especially in patients receiving treatment to greater than 10% of their body surface area. Patients should be warned about the possibility of sedation and cautioned against driving a motor vehicle or operating hazardous machinery while being treated with PRUDOXIN® Cream.

The sedating effects of alcoholic beverages, antihistamines, and other CNS depressants may be potentiated when PRUDOXIN® Cream is used.

If excessive drowsiness occurs it may be necessary to reduce the frequency of applications, the amount of cream applied, and/or the percentage of body surface area treated, or discontinue the drug. However, the efficacy with reduced frequency of applications has not been established.

Keep this product away from the eyes.

PRECAUTIONS

General Drowsiness: Since drowsiness may occur with the use of PRUDOXIN® Cream, patients should be warned of the possibility and cautioned against driving a car or operating dangerous machinery while using this drug. Patients should also be cautioned that their response to alcohol may be potentiated.

Sedating drugs may cause confusion and oversedation in the elderly; elderly patients generally should be observed closely for confusion and oversedation when started on PRUDOXIN® Cream. (See PRECAUTIONS - Geriatric Use.)

Use under occlusion: Occlusive dressings may increase the absorption of most topical drugs; therefore, occlusive dressings should not be utilized with PRUDOXIN® Cream.

Contact sensitization: Use of PRUDOXIN® Cream can cause Type IV hypersensitivity reactions (contact sensitization) to doxepin.

Drug Interactions

Studies have not been performed examining drug interactions with PRUDOXIN® Cream. However, since plasma levels of doxepin following topical application of PRUDOXIN® Cream can reach levels obtained with oral doxepin HCl therapy, the following drug interactions are possible following topical PRUDOXIN® Cream application:

Drugs Metabolized by P450 2D6: The biochemical activity of the drug metabolizing isozyme cytochrome P450 2D6 (debrisoquin hydroxylase) is reduced in a subset of the Caucasian population (about 7-10% of Caucasians are so-called "poor metabolizers"); reliable estimates of the prevalence of reduced P450 2D6 isozyme activity among Asian, African and other populations are not yet available.

Poor metabolizers have higher than expected plasma concentrations of tricyclic antidepressants (TCAs) when given usual doses. Depending on the fraction of drug metabolized by P450 2D6, the increase in plasma concentration may be small, or quite large (8-fold increase in plasma AUC of the TCA).

In addition, certain drugs inhibit the activity of this isozyme and make normal metabolizers resemble poor metabolizers. An individual who is stable on a given dosage regimen of a TCA may become abruptly toxic when given one of these inhibiting drugs as concomitant therapy. The drugs that inhibit cytochrome P450 2D6 include some that are not metabolized by the enzyme (quinidine; cimetidine) and many that are substrates for P450 2D6 (many other antidepressants, phenothiazines, and the Type 1C antiarrhythmics propafenone and flecainide). While all the selective serotonin reuptake inhibitors (SSRIs), e.g., fluoxetine, sertraline, and paroxetine, inhibit P450 2D6, they may vary in the extent of inhibition. The extent to which SSRI-TCA interactions may pose clinical problems will depend on the degree of inhibition and the pharmacokinetics of the SSRI involved. Nevertheless, caution is indicated in the co-administration of TCAs with any of the SSRIs. Of particular importance, sufficient time must elapse before initiating TCA treatment in a patient being withdrawn from fluoxetine, given the long half- life of the parent and active metabolite (at least 5 weeks may be necessary).

Concomitant use of tricyclic antidepressants with drugs that can inhibit cytochrome P450 2D6 may require lower doses than usually prescribed for either the tricyclic antidepressant or the other drug. It is desirable to monitor TCA plasma levels whenever a TCA is going to be co-administered with another drug known to be an inhibitor of P450 2D6.

MAO Inhibitors: Serious side effects and even death have been reported following the concomitant use of certain drugs with MAO inhibitors. Therefore, MAO inhibitors should be discontinued at least two weeks prior to the cautious initiation of therapy with PRUDOXIN® Cream. The exact length of time may vary and is dependent upon the particular MAO inhibitor being used, the length of time it has been administered, and the dosage involved.

Cimetidine: Serious anticholinergic symptoms (i.e., severe dry mouth, urinary retention and blurred vision) have been associated with elevations in the serum levels of tricyclic antidepressant when cimetidine therapy is initiated. Additionally, higher than expected tricyclic antidepressant levels have been observed when they are begun in patients already taking cimetidine.

Alcohol: Alcohol ingestion may exacerbate the potential sedative effects of PRUDOXIN® Cream. This is especially important in patients who may use alcohol excessively.

Tolazamide: A case of severe hypoglycemia has been reported in a type II diabetic patient maintained on tolazamide (1 gm/day) 11 days after the addition of oral doxepin (75 mg/day).

Carcinogenesis, Mutagenesis, Impairment of Fertility

Carcinogenesis, mutagenesis, and impairment of fertility studies have not been conducted with doxepin hydrochloride.

Pregnancy

Reproduction studies have been performed in which doxepin was orally administered to rats and rabbits at doses up to 0.6 and 1.2 times, respectively, the estimated exposure to doxepin that results from use of 16 grams of PRUDOXIN® Cream per day (four applications of four grams of cream per day; dose multiples reflect comparisons made following normalization of the data on the basis of body surface area estimates) and have revealed no evidence of harm to rat or rabbit fetuses due to doxepin. There are, however, no adequate and well-controlled studies in pregnant women. Because animal reproduction studies are not always predictive of human response, this drug should be used during pregnancy only if clearly needed.

Nursing Mothers

Doxepin is excreted in human milk after oral administration. It is possible that doxepin may also be excreted in human milk following topical application of PRUDOXIN® Cream.

One case has been reported of apnea and drowsiness in a nursing infant whose mother was taking an oral dosage form of doxepin HCl.

Because of the potential for serious adverse reactions in nursing infants from doxepin, a decision should be made whether to discontinue nursing or to discontinue the drug, taking into account the importance of the drug to the mother.

Pediatric Use

The use of PRUDOXIN® Cream in pediatric patients is not recommended. Safe conditions for use of PRUDOXIN® Cream in children have not been established. One case has been reported of a 2.5 year old child who developed somnolence, grand mal seizure, respiratory depression, ECG abnormalities, and coma after treatment with PRUDOXIN® Cream. A total of 27 grams had been applied over three days for eczema. He was treated with supportive care, activated charcoal, and systemic alkalization and recovered.

Geriatric Use

Clinical studies of PRUDOXIN® Cream did not include sufficient numbers of subjects aged 65 and over to determine whether they respond differently from younger subjects. Other reported clinical experience has not identified differences in responses between the elderly and younger patients. In general, dose selection for an elderly patient should be cautious, usually starting at the low end of the dosing range, reflecting the greater frequency of decreased hepatic, renal or cardiac function, and of concomitant disease or other drug therapy.

The extent of renal excretion of doxepin has not been determined. Because elderly patients are more likely to have decreased renal function, care should be taken in dose selections.

Sedating drugs may cause confusion and oversedation in the elderly; elderly patients generally should be observed closely for confusion and oversedation when started on PRUDOXIN® Cream. (See WARNINGS.) An 80-year old male nursing home patient developed probable systemic anticholinergic toxicity which included urinary retention and delirium after PRUDOXIN® Cream had been applied to his arms, legs and back three times daily for two days.

ADVERSE REACTIONS

Controlled Clinical Trials

Systemic Adverse Effects: In controlled clinical trials of patients treated with PRUDOXIN® Cream, the most common systemic adverse event reported was drowsiness. Drowsiness occurred in 71 of 330 (22%) of patients treated with PRUDOXIN® Cream compared to 7 of 334 (2%) of patients treated with vehicle cream. Drowsiness resulted in the premature discontinuation of the drug in approximately 5% of patients treated with PRUDOXIN® Cream in controlled clinical trials.

Local Site Adverse Effects: In controlled clinical trials of patients treated with PRUDOXIN® Cream, the most common local site adverse event reported was burning and/or stinging at the site of application.

These occurred in 76 of 330 (23%) of patients treated with PRUDOXIN® Cream compared to 54 of 334 (16%) of patients treated with vehicle cream. Most of these reactions were categorized as "mild"; however, approximately 25% of patients who reported burning and/or stinging reported the reaction as "severe". Four patients treated with PRUDOXIN® Cream withdrew from the study because of the burning and/or stinging.

The table below presents the adverse events reported at an incidence of ≥ 1 % in either PRUDOXIN® or vehicle cream treatment groups during the trials:

Adverse Event | PRUDOXIN® N=330 | Vehicle N=334
Burning /Stinging | 76 (23.0%) | 54 (16.2%)
Drowsiness | 71 (21.5%) | 7 (2.1%)
Dry Mouth^1 | 32 (9.7%) | 4 (1.2%)
Pruritus^2 | 13 (3.9%) | 20 (6.0%)
Fatigue/Tiredness | 10 (3.0%) | 5 (1.5%)
Exacerbated Eczema | 10 (3.0%) | 8 (2.4%)
Other Application Site Reaction^3 | 10 (3.0%) | 16 (4.8%)
Dizziness^4 | 7 (2.1%) | 3 (0.9%)
Mental/Emotional Changes | 6 (1.8%) | 1 (0.3%)
Taste Perversion^5 | 5 (1.5%) | 1 (0.3%)
Edema | 4 (1.2%) | 1 (0.3%)
Headache | 3 (0.9%) | 14 (4.2%)
^1Includes reports of “dry lips”, “dry throat”, and “thirst”
^2Includes reports of “pruritus exacerbated”
^3Includes report of “increased irritation at application site”
^4Includes reports of “lightheadedness” and “dizziness/vertigo”
^5Includes reports of “bitter taste” and “metallic taste in mouth”

Adverse events occurring in 0.5% to < 1.0% of PRUDOXIN® Cream treated patients in the controlled clinical trials included: nervousness/anxiety, tongue numbness, fever, and nausea.

Post-Marketing Experience

Twenty-six cases of allergic contact dermatitis have been reported in patients using PRUDOXIN® Cream, twenty of which were documented by positive patch test to doxepin 5% cream.

OVERDOSAGE

Deaths may occur from overdosage with this class of drugs. As the management is complex and changing, it is recommended that the physician contact a poison control center for current information on treatment. Signs and symptoms of toxicity develop rapidly after tricyclic antidepressant overdose; therefore, hospital monitoring is required as soon as possible.

Manifestations

Should overdosage with topical application of PRUDOXIN® Cream occur, the signs and symptoms may include: cardiac dysrhythmias, severe hypotension, convulsions, and CNS depression, including coma. Changes in the electrocardiogram, particularly in QRS axis or width, are clinically significant indicators of tricyclic antidepressant toxicity.

Other signs of overdose may include: confusion, disturbed concentration, transient visual hallucinations, dilated pupils, agitation, hyperactive reflexes, stupor, drowsiness, muscle rigidity, vomiting, hypothermia, hyperpyrexia, or any of the symptoms listed under ADVERSE REACTIONS.

General Recommendations

General: Obtain an ECG and immediately initiate cardiac monitoring. Protect the patient's airway, establish an intravenous line and initiate gastric decontamination. A minimum of six hours of observation with cardiac monitoring and observation for signs of CNS or respiratory depression, hypotension, cardiac dysrhythmias and/or conduction blocks, and seizures is strongly advised. If signs of toxicity occur at any time during this period, extended monitoring is recommended. There are case reports of patients succumbing to fatal dysrhythmias late after overdose; these patients had clinical evidence of significant poisoning prior to death and most received inadequate gastrointestinal decontamination.

Monitoring of plasma drug levels should not guide management of the patient.

Cardiovascular: A maximal limb-lead QRS duration of ≥ 0.10 seconds may be the best indication of the severity of the overdose. Intravenous sodium bicarbonate should be used to maintain the serum pH in the range of 7.45 to 7.55. If the pH response is inadequate, hyperventilation may also be used. Concomitant use of hyperventilation and sodium bicarbonate should be done with extreme caution, with frequent pH monitoring. A pH>7.60 or a pCO2 <20 mm Hg is undesirable. Dysrhythmias unresponsive to sodium bicarbonate therapy/hyperventilation may respond to lidocaine, bretylium or phenytoin. Type 1A and 1C antiarrhythmics are generally contraindicated (e.g., quinidine, disopyramide, and procainamide).

In rare instances, hemoperfusion may be beneficial in acute refractory cardiovascular instability in patients with acute toxicity. However, hemodialysis, peritoneal dialysis, exchange transfusions, and forced diuresis generally have been reported as ineffective in tricyclic antidepressant poisoning.

CNS: In patients with CNS depression, early intubation is advised because of the potential for abrupt deterioration. Seizures should be controlled with benzodiazepines, or if these are ineffective, other anticonvulsants (e.g., phenobarbital, phenytoin). Physostigmine is not recommended except to treat life- threatening symptoms that have been unresponsive to other therapies, and then only in consultation with a poison control center.

Pediatric Management: The principles of management of child and adult overdosages are similar. It is strongly recommended that the physician contact the local poison control center for specific pediatric treatment.

DOSAGE AND ADMINISTRATION

A thin film of PRUDOXIN® Cream should be applied four times each day with at least a 3 to 4 hour interval between applications. There are no data to establish the safety and effectiveness of PRUDOXIN® Cream when used for greater than 8 days. Chronic use beyond eight days may result in higher systemic levels and should be avoided. Use of PRUDOXIN® Cream for longer than 8 days may result in an increased likelihood of contact sensitization.

The risk for sedation may increase with greater body surface area application of PRUDOXIN® Cream (See WARNINGS section). Clinical experience has shown that drowsiness is significantly more common in patients applying PRUDOXIN® Cream to over 10% of body surface area; therefore, patients with greater than 10% of body surface area (see WARNINGS section) affected should be particularly cautioned concerning possible drowsiness and other systemic adverse effects of doxepin. If excessive drowsiness occurs, it may be necessary to do one or more of the following: reduce the body surface area treated, reduce the number of applications per day, reduce the amount of cream applied, or discontinue the drug.

Occlusive dressings may increase the absorption of most topical drugs; therefore, occlusive dressings should not be utilized with PRUDOXIN® Cream.

HOW SUPPLIED

PRUDOXIN® Cream is available containing 50 mg of doxepin hydrochloride, USP equivalent to 44.3 mg of doxepin. PRUDOXIN® Cream, 5% is a soft white cream available as follows:

NDC 0378-8130-45
carton containing one 45 g tube

Store below 27° C (80° F).

Manufactured for:
Mylan Pharmaceuticals Inc.
Morgantown, WV 26505 U.S.A.

Manufactured by:
DPT Laboratories, Ltd.
San Antonio, TX 78215 U.S.A.

PRUDOXIN is a registered trademark of Delcor Asset Corporation, a Mylan Company

©2017 Mylan Pharmaceuticals Inc.

DPT:PRUD:R1
Revised: 6/2017

140901-0617

PRINCIPAL DISPLAY PANEL – 5%

NDC 0378-8130-45

PRUDOXIN®
(doxepin hydrochloride)
Cream
5%

For Topical Dermatologic Use Only

Rx only Net Wt. 45 g

Warnings: For External Use Only. Not For Oral, Intravaginal or Ophthalmic Use. Keep away from eyes.

Keep this and all medication out of the reach of children.

Directions: Apply a thin film of PRUDOXIN® Cream four times each day with at least a 3 to 4 hour interval between applications. If excessive drowsiness occurs it may be necessary to do one or more of the following: reduce the body surface area treated, reduce the number of applications per day, reduce the amount of cream applied, or discontinue the drug.

Refer to product insert for prescribing information and inactive ingredient listing.

Store below 27ºC (80ºF).

Warnings: For External Use Only. Not For Oral, Intravaginal or Ophthalmic Use.

Keep away from eyes. Keep this and all medication out of the reach of children.

Contains: Doxepin hydrochloride, USP, 5% (equivalent to 4.4% doxepin) in a vehicle of sorbitol, cetyl alcohol, isopropyl myristate, glyceryl stearate, PEG-100 stearate, petrolatum, benzyl alcohol, titanium dioxide and purified water.

Manufactured for:
Mylan Pharmaceuticals Inc.
Morgantown, WV 26505 U.S.A.

Manufactured by:
DPT Laboratories, Ltd.
San Antonio, TX 78215 U.S.A.

PRUDOXIN is a registered
trademark of Delcor Asset
Corporation, a Mylan Company

©2017 Mylan Pharmaceuticals Inc.

DPT:8130:45:1C:R1

Mylan.com